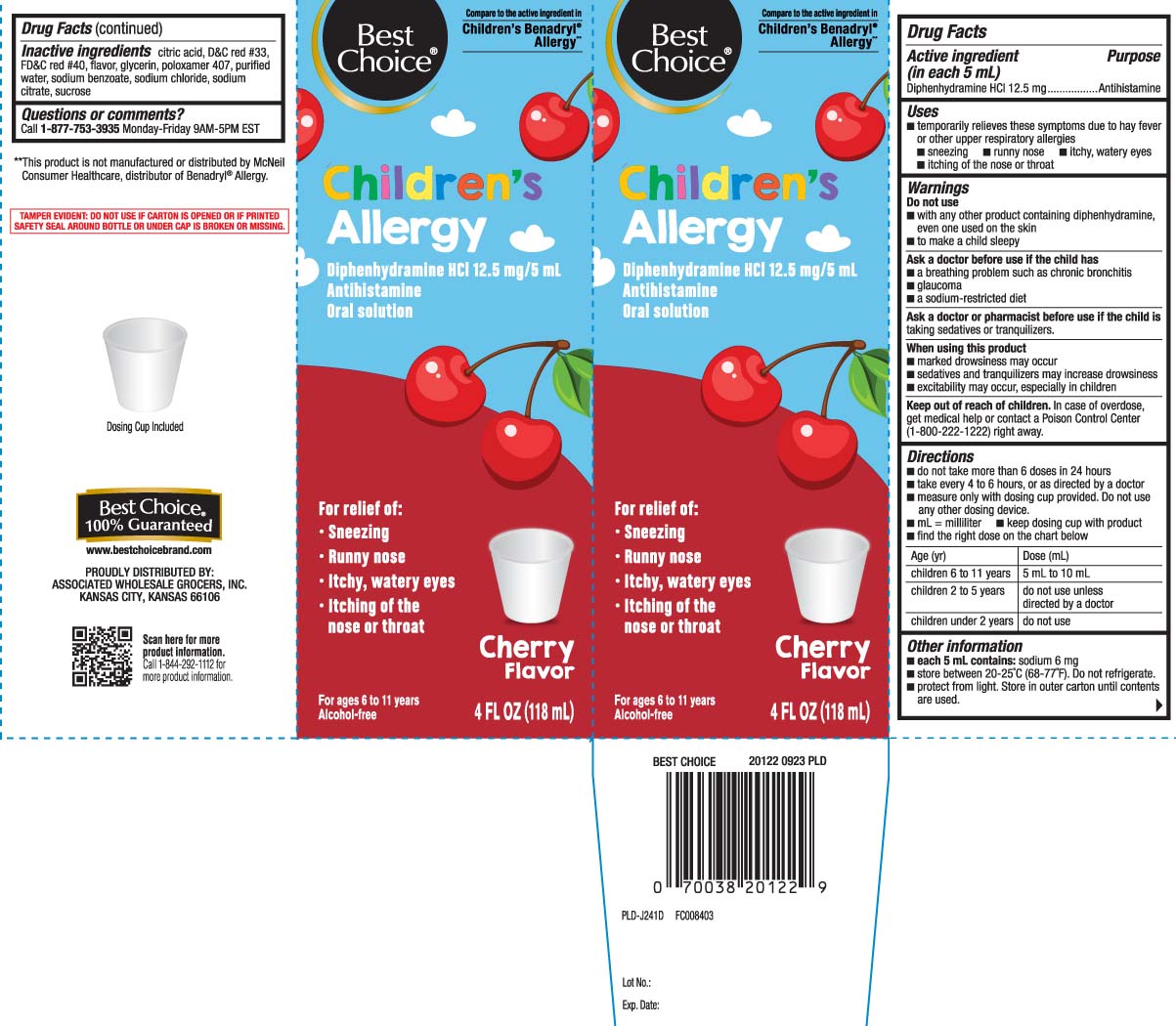 DRUG LABEL: Childrens Allergy
NDC: 63941-292 | Form: LIQUID
Manufacturer: Best Choice  (Valu Merchandisers Company)
Category: otc | Type: HUMAN OTC DRUG LABEL
Date: 20260224

ACTIVE INGREDIENTS: DIPHENHYDRAMINE HYDROCHLORIDE 12.5 mg/5 mL
INACTIVE INGREDIENTS: ANHYDROUS CITRIC ACID; GLYCERIN; WATER; D&C RED NO. 33; SODIUM BENZOATE; SUCROSE; FD&C RED NO. 40; POLOXAMER 407; SODIUM CHLORIDE; TRISODIUM CITRATE DIHYDRATE

Drug Facts

Active ingredient (in each 5 mL)

Diphenhydramine HCl 12.5 mg

Purpose

Antihistamine

Uses

temporarily relieves these symptoms due to hay fever or other upper respiratory allergies:

- runny nose
- sneezing
- itchy, watery eyes
- itching of the nose or throat

Warnings

Do not use

- with any other product containing diphenhydramine, even one used on the skin
- to make a child sleepy

Ask a doctor before use if the child has

- a breathing problem such as chronic bronchitis
- glaucoma
- a sodium restricted diet

Ask a doctor or pharmacist before use if the child is

taking sedatives or tranquilizers

When using this product

- marked drowsiness may occur
- sedatives and tranquilizers may increase drowsiness
- excitability may occur, especially in children

Keep out of reach of children.

In case of overdose, get medical help or contact a Poison Control Center (1-800-222-1222) right away.

Directions

- do not take more than 6 doses in 24 hours
- take every 4 to 6 hours, or as directed by a doctor
- measure only with dosing cup provided. Do not use any other dosing device
- mL = milliliter
- keep dosing cup with product
- find the right dose on the chart below

age (yr) | Dose (mL)
children 6 to 11 years | 5 mL to 10 mL
children 2 to 5 years | do not use unless directed by a doctor
children under 2 years | do not use

Other information

- each 5 mL contains: sodium 6 mg
- store between 20-25ºC (68-77ºF). Do not refrigerate
- Protect from light. Store in outer carton until contents are used.

Inactive ingredients

anhydrous citric acid, D&C red #33, FD&C red #40, flavor, glycerin, poloxamer 407, purified water, sodium benzoate, sodium chloride, sodium citrate, sucrose

Questions or comments?

Call 1-877-753-3935 Monday-Friday 9AM-5PM EST

Principal Display Panel

Compare to the active ingredient in Children's Benadryl® Allergy**

Children's Allergy

Diphenhydramine HCl 12.5 mg/5 mL

Antihistamine

Oral Solution

For relief of:

- Sneezing
- Runny nose
- Itchy, water eyes
- Itchy of the nose or throat

Cherry Flavor

For ages 6 to 11 years

Alcohol Free

FL OZ (mL)

Dosing Cup Included

*This product is not manufactured or distributed by McNeil Consumer Healthcare, Inc., distributor of Benadryl® Allergy.

TAMPER EVIDENT: DO NOT USE IF IF CARTON IS OPENED OR IF PRINTED SAFETY SEAL AROUND BOTTLE OR UNDER CAP IS BROKEN OR MISSING.

PROUDLY DISTRIBUTED BY:

ASSOCIATED WHOLESALE GROCERS, INC.

KANSAS CITY, KANSAS 66106

Package Label

BEST CHOICE Children's Allergy Cherry Flavor